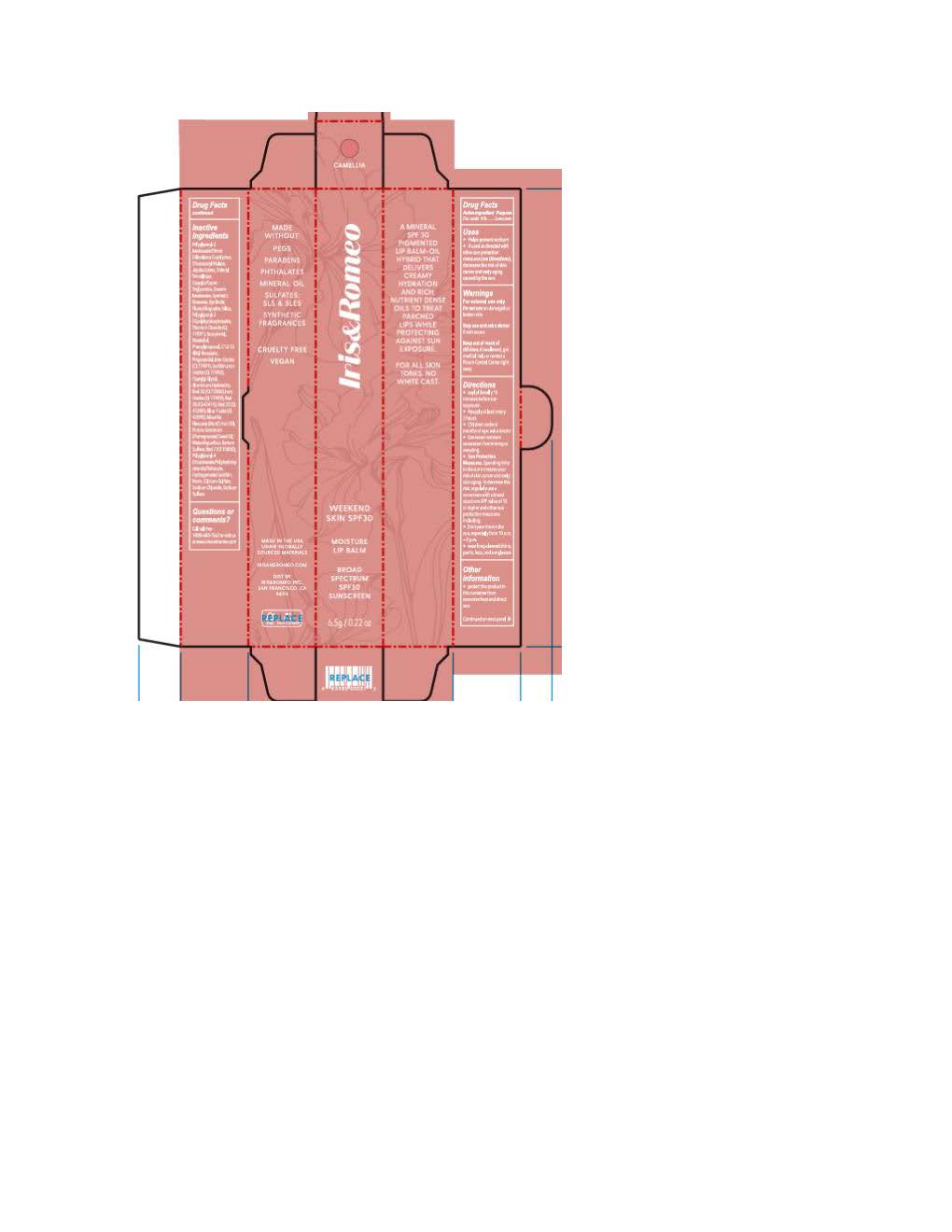 DRUG LABEL: Iris and Romeo Weekend Skin Moisture Lip Balm
NDC: 83247-6319 | Form: LOTION
Manufacturer: Iris and Romeo
Category: otc | Type: HUMAN OTC DRUG LABEL
Date: 20251112

ACTIVE INGREDIENTS: ZINC OXIDE 110 mg/1 mL
INACTIVE INGREDIENTS: RED 28; RED 40; TOCOPHEROL; SODIUM CHLORIDE; FERROSOFERRIC OXIDE; PHENYLPROPANOL; FERRIC OXIDE RED; ALKYL (C12-15) BENZOATE; CAPRYLIC/CAPRIC TRIGLYCERIDE; CAPRYLYL GLYCOL; POLYGLYCERYL-4 DIISOSTEARATE/POLYHYDROXYSTEARATE/SEBACATE; WATER; CALCIUM SULFATE; ROSIN; PROPANEDIOL; BLUE 1 LAKE; TRIDECYL TRIMELLITATE; ALUMINUM HYDROXIDE; TIN OXIDE; CI 77891; RED 33; SODIUM SULFATE; SYNTHETIC BEESWAX; DIISOSTEARYL MALATE; HYDROLYZED JOJOBA ESTERS (ACID FORM); MAURITIA FLEXUOSA FRUIT OIL; FERRIC OXIDE YELLOW; .ALPHA.-BISABOLOL, (+)-; SILICON DIOXIDE; POLYGLYCERYL-2 DIPOLYHYDROXYSTEARATE; RED 7; MICA; PUNICA GRANATUM SEED OIL; LECITHIN, SOYBEAN

Iris and Romeo Weekend Skin Moisture Lip Balm